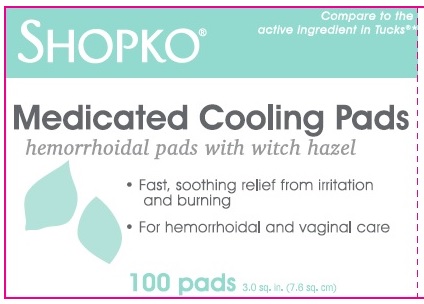 DRUG LABEL: SHOPKO Medicated Cooling
NDC: 37012-211 | Form: SWAB
Manufacturer: Shopko Stores Operating Co., LLC.
Category: otc | Type: HUMAN OTC DRUG LABEL
Date: 20190201

ACTIVE INGREDIENTS: WITCH HAZEL 50 g/100 g
INACTIVE INGREDIENTS: WATER; GLYCERIN; PROPYLENE GLYCOL; DECYL GLUCOSIDE; CITRIC ACID MONOHYDRATE; PHENOXYETHANOL; SODIUM BENZOATE; ALOE ARBORESCENS LEAF; POTASSIUM SORBATE; ALCOHOL

SHOPKO Medicated Cooling Pads

Active Ingredient

Witch hazel 50%

Purpose

Astringent

Uses

- helps relieve the local itching and discomfort associated with hemorrhoids
- temporary relief of irritation and burning.
- aids in protecting irritated anorectal areas.

Warnings

For external use only.

When using this product

- do not exceed the recommended daily dosage unless directed by a doctor
- do not put this product into the rectum by using fingers or any mechanical device or applicator.

Stop use and ask a doctor if

- bleeding occurs
- condition worsens or does not improve within 7 days

Keep out of reach of children

If swallowed, get medical help or contact a Poison Control Center right away.(1-800-222-1222)

If pregnant or breast-feeding

Ask a health professional before use

Directions

- adult: cleanse the area by gently wiping, patting or blotting. If necessary, repeat until all matter is removed from the area.
- use up to 6 times daily or after each bowel movement and before applying hemorrhoidal treatments, and then discard

- children under 12 years of age: consult a doctor

- Dispose of pad in trash after use.Do not flush

Other information

- store at room temperature 15-30^0C (59-86°F)
- for vaginal care - cleanse the area by gently wiping, patting, or blotting. Repeat as needed.
- for use as moist compress - if necessary, first cleanse the area as previously described. Fold wipe to desired size and place in contact with tissue for a soothing and cooling effect. Leave in place for 15 minutes and repeat as needed.

Inactive Ingredients

Alcohol, Aloe, citric acid, Decyl Glucoside, Glycerin, Phenoxyethanol, Potassium Sorbate, Propylene Glycol, Sodium Benzoate, Water.

Principal Display Panel

SHOPKO

Compared to the active ingredients in Tucks*

Medicated Cooling Pads

hemorrhoidal pads with witch hazel

- Fast, soothing relief from Irritation and burning
- For hemmorhoidal and vaginal care

100 pads 3.0 sq. in. (7.6 sq. cm)